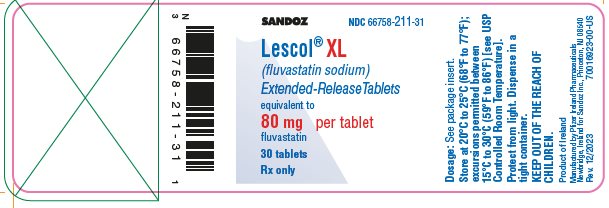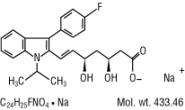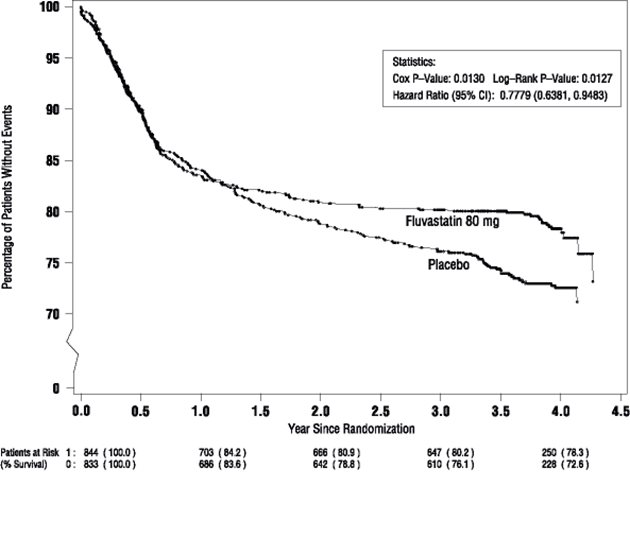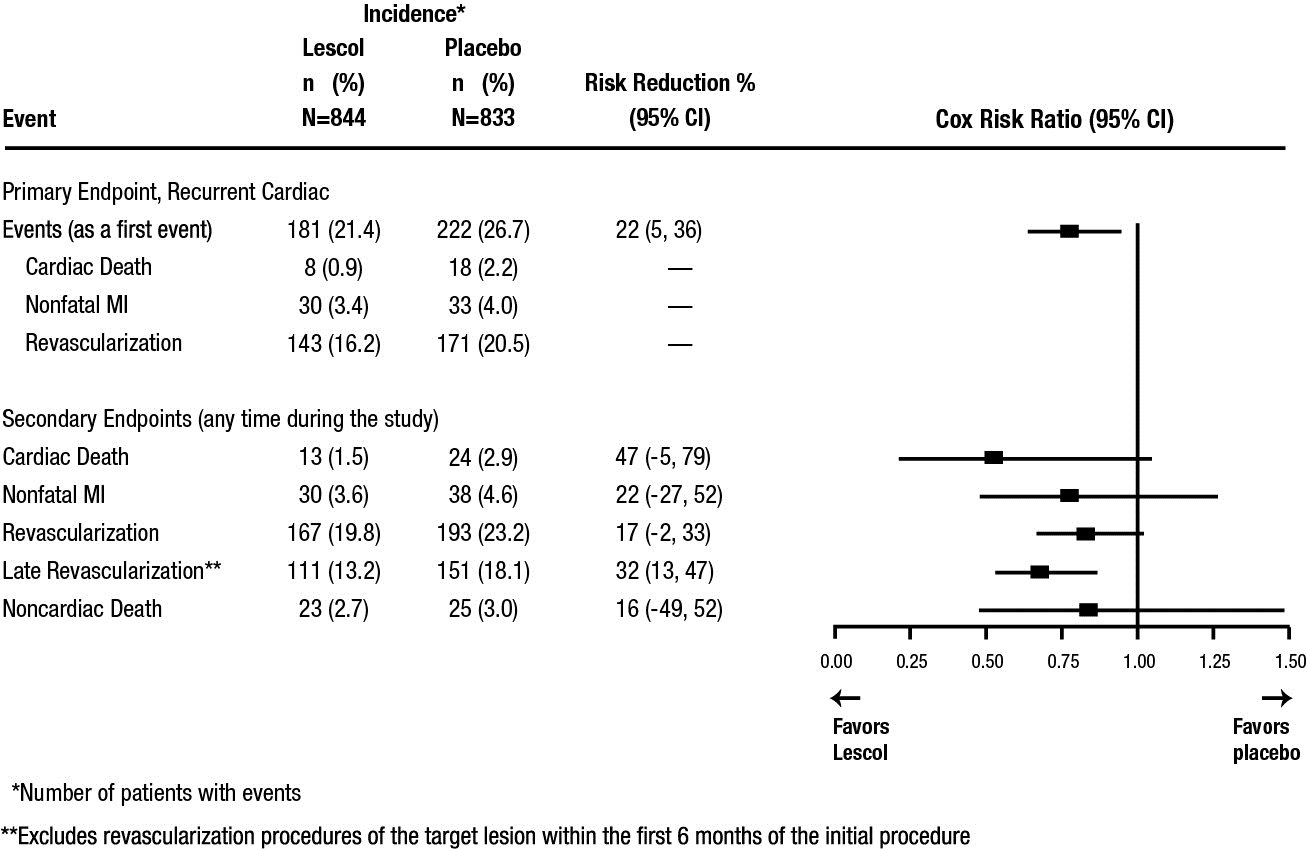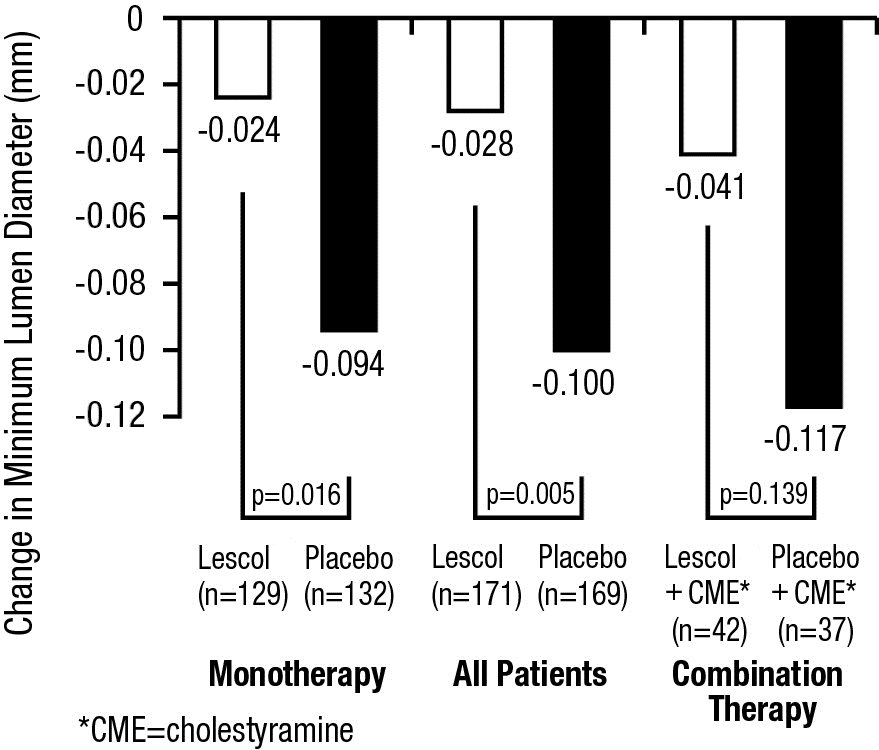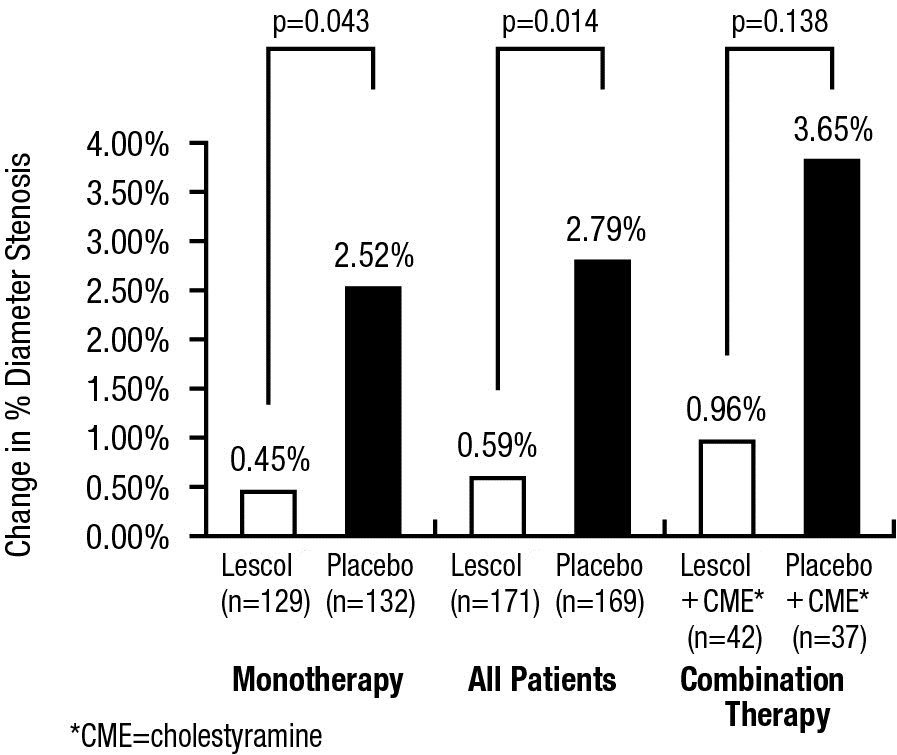 DRUG LABEL: Lescol
NDC: 66758-211 | Form: TABLET, EXTENDED RELEASE
Manufacturer: Sandoz Inc
Category: prescription | Type: HUMAN PRESCRIPTION DRUG LABEL
Date: 20231213

ACTIVE INGREDIENTS: FLUVASTATIN SODIUM 80 mg/1 1
INACTIVE INGREDIENTS: HYDROXYPROPYL CELLULOSE (1600000 WAMW); HYPROMELLOSE 2208 (15000 MPA.S); FERRIC OXIDE YELLOW; MAGNESIUM STEARATE; MICROCRYSTALLINE CELLULOSE; POLYETHYLENE GLYCOL 8000; POTASSIUM BICARBONATE; POVIDONE, UNSPECIFIED; TITANIUM DIOXIDE

HIGHLIGHTS OF PRESCRIBING INFORMATION

These highlights do not include all the information needed to use Lescol® XL safely and effectively. See full prescribing information for Lescol® XL.
Lescol® XL (fluvastatin) extended-release tablets, for oral use
Initial U.S. Approval: 1993

RECENT MAJOR CHANGES

Contraindications, Pregnancy and Lactation (4) Removed 11/2023

1 INDICATIONS AND USAGE

LESCOL XL is indicated (1):

- To reduce the risk of undergoing coronary revascularization procedures and slow the progression of coronary atherosclerosis in adults with clinically evident coronary heart disease.
- As an adjunct to diet to reduce low-density lipoprotein cholesterol (LDL-C) in adults with primary hyperlipidemia.
- As an adjunct to diet to reduce LDL-C in adults and pediatric patients 10 years of age and older with heterozygous familial hypercholesterolemia (HeFH) who require 80 mg

2 DOSAGE AND ADMINISTRATION

- LESCOL XL can be taken with or without food and may be taken at any time of the day. (2.1)
- Do not break, crush or chew LESCOL XL tablets prior to administration. (2.1)
- Adults: The recommended starting dose is 80 mg (administered as one 80 mg LESCOL XL once daily). (2.2)
Children: The recommended dose is 80 mg once daily in pediatric patients 10 years of age and older who require 80 mg of fluvastatin. LESCOL XL is not recommended for dosage initiation in pediatric patients because the recommended starting dosage cannot be achieved with the available strength of 80 mg. (2.3)

3 DOSAGE FORMS AND STRENGTHS

Extended-release tablets: 80 mg of fluvastatin (3)

4 CONTRAINDICATIONS

- Acute liver failure or decompensated cirrhosis (4)
- Hypersensitivity to fluvastatin or any excipient in LESCOL XL (4)

5 WARNINGS AND PRECAUTIONS

- Myopathy and Rhabdomyolysis: Risk factors include age 65 years or greater, uncontrolled hypothyroidism, renal impairment, and concomitant use with certain other drugs. Discontinue LESCOL XL if markedly elevated creatine kinase (CK) levels occur, or myopathy is diagnosed or suspected. Temporarily discontinue LESCOL XL in patients experiencing an acute or serious condition at high risk of developing renal failure secondary to rhabdomyolysis. Inform patients of the risk of myopathy and rhabdomyolysis when starting or increasing LESCOL XL dosage. Instruct patients to promptly report unexplained muscle pain, tenderness, or weakness, particularly if accompanied by malaise or fever. (5.1)
- Immune-Mediated Necrotizing Myopathy (IMNM): Rare reports of IMNM, an autoimmune myopathy, have been reported with statin use. Discontinue LESCOL XL if IMNM is suspected.(5.2)
- Hepatic Dysfunction: Increases in serum transaminases have occurred, some persistent. Rare reports of fatal and non-fatal hepatic failure have occurred. Consider testing liver enzyme before initiating therapy and as clinically indicated thereafter. If serious hepatic injury with clinical symptoms and/or hyperbilirubinemia or jaundice occurs, promptly discontinue LESCOL XL (5.3)

6 ADVERSE REACTIONS

Most frequent adverse reactions occurring in ≥ 2.5% of subjects treated with LESCOL XL and more than placebo are: influenza-like symptoms, sinusitis, dyspepsia, urinary tract infection, bronchitis, and nausea. (6.1)

To report SUSPECTED ADVERSE REACTIONS, contact Sandoz Inc. at 1-800-525-8747 or FDA at 1-800-FDA-1088 or www.fda.gov/medwatch.

7 DRUG INTERACTIONS

- Gemfibrozil: Avoid use with LESCOL XL. (7.1)
- Cyclosporine and Fluconazole: Avoid use with LESCOL XL. (7.1)
- Fibrates, Lipid-modifying doses (≥ 1 g/day) of Niacin, and Colchicine: Consider if the benefit of concomitant use with LESCOL XL outweighs the increased risk of myopathy and rhabdomyolysis. If concomitant use is decided, monitor patients for signs and symptoms of myopathy, particularly during initiation of therapy and during upward dose titration. (7.1)
- Warfarin: Obtain an International Normalized Ratio (INR) before starting and frequently enough after initiation or discontinuation to ensure that no significant alteration in INR occurs. Once the INR is stable, monitor INR at regular intervals. (7.2)
- Glyburide: Monitor blood glucose levels when LESCOL XL is initiated. (7.2)
- Phenytoin: Monitor plasma phenytoin levels when LESCOL XL treatment is initiated. (7.2)

8 USE IN SPECIFIC POPULATIONS

- Pregnancy: May cause fetal harm (8.1)
- Lactation: Breastfeeding not recommended during treatment with LESCOL XL (8.2)

FULL PRESCRIBING INFORMATION

1 INDICATIONS AND USAGE

LESCOL XL is indicated:

- To reduce the risk of undergoing coronary revascularization procedures and slow the progression of coronary atherosclerosis in adults with clinically evident coronary heart disease.
- As an adjunct to diet to reduce low-density lipoprotein cholesterol (LDL-C) in adults with primary hyperlipidemia.
- As an adjunct to diet to reduce LDL-C in adults and pediatric patients 10 years of age and older with heterozygous familial hypercholesterolemia (HeFH) who require 80 mg of fluvastatin daily.

2 DOSAGE AND ADMINISTRATION

2.1 Important Dosage Information

- Take LESCOL XL tablets orally once daily as a single dose, with or without food.
- Do not break, crush, or chew LESCOL XL tablets.
- LESCOL XL is only available as an 80 mg tablet. LESCOL XL cannot be titrated [see Dosage and Administration (2.2, 2.3)].
- For patients that require a high-intensity statin or are unable to achieve their LDL-C goal receiving LESCOL XL 80 mg daily, prescribe alternative LDL-C-lowering treatment.
- Assess LDL-C when clinically appropriate, as early as 4 weeks after initiating LESCOL XL.

2.2 Recommended Dosage in Adult Patients

The recommended dosage for LESCOL XL is 80 mg once daily.

2.3 Recommended Dosage in Pediatric Patients Aged 10 Years of Age and Older with HeFH

LESCOL XL is not recommended for dosage initiation in pediatric patients because the recommended starting dosage cannot be achieved with the available strength of 80 mg. Recommend use of another fluvastatin product to initiate dosing in pediatric patients.

The recommended dosage of LESCOL XL is 80 mg once daily in pediatric patients 10 years of age and older who require 80 mg of fluvastatin.

3 DOSAGE FORMS AND STRENGTHS

Extended-release tablets: 80 mg of fluvastatin: yellow, round, slightly biconvex film-coated tablets with beveled edges debossed with “LESCOL XL” on one side and “80” on the other.

4 CONTRAINDICATIONS

LESCOL XL is contraindicated in patients with:

- Acute liver failure or decompensated cirrhosis [see Warnings and Precautions (5.3)].
- Hypersensitivity to fluvastatin or any of the excipients in LESCOL XL. Hypersensitivity reactions, including anaphylaxis, angioedema, and Stevens-Johnson syndrome have been reported [see Adverse Reactions (6.2)].

5 WARNINGS AND PRECAUTIONS

5.1 Myopathy and Rhabdomyolysis

LESCOL XL may cause myopathy (muscle pain, tenderness, or weakness associated with elevated creatine kinase [CK]) and rhabdomyolysis. Acute kidney injury secondary to myoglobinuria and rare fatalities have occurred as a result of rhabdomyolysis with statins, including LESCOL XL.

Myopathy, defined as muscle aching or muscle weakness in conjunction with increases in CK, values to greater than 10 times the upper limit of normal (ULN) was < 0.1% in fluvastatin clinical trials [see Adverse Reactions (6.1)].

Risk Factors for Myopathy

Risk factors for myopathy include age 65 years or greater, uncontrolled hypothyroidism, renal impairment, and concomitant use with certain other drugs (including other lipid-lowering therapies) [see Drug Interactions (7.1)].

Steps to Prevent or Reduce the Risk of Myopathy and Rhabdomyolysis

Avoid concomitant use of LESCOL XL with gemfibrozil, cyclosporin, and fluconazole. When used concomitantly with LESCOL XL, lipid modifying doses (≥ 1 g/day) of niacin, fibrates, and colchicine may also increase the risk of myopathy and rhabdomyolysis [see Drug Interactions (7.1)].

Discontinue LESCOL XL if markedly elevated CK levels occur or if myopathy is either diagnosed or suspected. Muscle symptoms and CK increases may resolve if LESCOL XL is discontinued. Temporarily discontinue LESCOL XL in patients experiencing an acute or serious condition at high risk of developing renal failure secondary to rhabdomyolysis, e.g., sepsis, shock, severe hypovolemia, major surgery, trauma, severe metabolic, endocrine, or electrolyte disorders, or uncontrolled epilepsy.

Inform patients of the risk of myopathy and rhabdomyolysis when starting LESCOL XL. Instruct patients to promptly report any unexplained muscle pain, tenderness, or weakness, particularly if accompanied by malaise or fever.

5.2 Immune-Mediated Necrotizing Myopathy

There have been rare reports of immune-mediated necrotizing myopathy (IMNM), an autoimmune myopathy, associated with statin use, including reports of recurrence when the same or a different statin was administered. IMNM is characterized by proximal muscle weakness and elevated serum CK, which persist despite discontinuation of statin treatment; positive anti-HMG CoA reductase antibody, muscle biopsy showing necrotizing myopathy, and improvement with immunosuppressive agents. Additional neuromuscular and serologic testing may be necessary. Treatment with immunosuppressive agents may be required. Discontinue LESCOL XL if IMNM is suspected.

5.3 Hepatic Dysfunction

Increases in serum transaminases have been reported with use of LESCOL XL [see Adverse Reactions (6.1)]. In most cases, these changes appeared soon after initiation, were transient, were not accompanied by symptoms, and resolved or improved on continued therapy or after a brief interruption in therapy. Persistent increases to more than three times the ULN in serum transaminases have occurred in approximately 1.1% of patients receiving fluvastatin in clinical trials. Marked persistent increases of hepatic transaminases have also occurred with fluvastatin. There have been rare post-marketing reports of fatal and non-fatal hepatic failure in patients taking statins, including LESCOL XL.

Patients who consume substantial quantities of alcohol and/or have a history of liver disease may be at increased risk for hepatic injury.

Consider liver enzyme testing before LESCOL XL initiation and thereafter, when clinically indicated. LESCOL XL is contraindicated in patients with acute liver failure or decompensated cirrhosis [see Contraindications (4)]. If serious hepatic injury with clinical symptoms and/or hyperbilirubinemia or jaundice occurs, promptly discontinue LESCOL XL.

5.4 Increases in HbA1c and Fasting Serum Glucose Levels

Increases in HbA1c and fasting serum glucose levels have been reported with statins, including LESCOL XL. Optimize lifestyle measures, including regular exercise, maintaining a healthy body weight, and making healthy food choices.

6 ADVERSE REACTIONS

The following serious adverse reactions are discussed in greater detail in other sections of the label:

- Myopathy and Rhabdomyolysis [see Warnings and Precautions (5.1)]
- Immune-Mediated Necrotizing Myopathy [see Warnings and Precautions (5.2)]
- Hepatic Dysfunction [see Warnings and Precautions (5.3)]
- Increases in HbA1c and Fasting Serum Glucose Levels [see Warnings and Precautions (5.4)]

6.1 Clinical Trials Experience

Because clinical trials are conducted under widely varying conditions, adverse reaction rates observed in the clinical trials of a drug cannot be directly compared to rates in the clinical trials of another drug and may not reflect the rates observed in practice.

In the fluvastatin capsule, clinical trials there were 2326 patients treated with fluvastatin (age range, 18 to 75 years, 44% women, 94% White, 4% Black or African American, 2% other ethnicities) with a median treatment duration of 24 weeks. The most common adverse reactions that led to treatment discontinuation and occurred at an incidence greater than placebo were: transaminase increased (0.8%), upper abdominal pain (0.3%), dyspepsia (0.3%), fatigue (0.2%), and diarrhea (0.2%).

In the LESCOL XL clinical trials there were 912 patients treated with LESCOL XL (age range, 21 to 87 years, 52% women, 91% White, 4% Black of African American, 5% other ethnicities) with a median treatment duration of 24 weeks. The most common adverse reactions that led to treatment discontinuation were abdominal pain (0.7%), diarrhea (0.5%), nausea (0.4%), dyspepsia (0.4%) and chest pain (0.3%).

Adverse reactions occurring in the fluvastatin capsules and LESCOL XL controlled trials with a frequency ≥ 2% included the following:

Table 1. Adverse Reactions Reported in ≥ 2% in Patients Treated with Fluvastatin Capsules/LESCOL XL and at an Incidence Greater Than Placebo in Placebo-Controlled Trials Pooled Dosages
Adverse reaction | Placeboa; N = 960; (%) | Fluvastatin capsulesa; N = 2326; (%) | LESCOL XLb; N = 912; (%)
Influenza-like symptoms | 5.7 | 5.1 | 7.1
Headache | 7.8 | 8.9 | 4.7
Myalgia | 4.5 | 5.0 | 3.8
Abdominal pain | 3.8 | 4.9 | 3.7
Dyspepsia | 3.2 | 7.9 | 3.5
Sinusitis | 1.9 | 2.6 | 3.5
Diarrhea | 4.2 | 4.9 | 3.3
Arthropathy | NA | NA | 3.2
Urinary tract infection | 1.1 | 1.6 | 2.7
Nausea | 2.0 | 3.2 | 2.5
Bronchitis | 1.0 | 1.8 | 2.6
Fatigue | 2.3 | 2.7 | 1.6
Flatulence | 2.5 | 2.6 | 1.4
Arthritis | 2.0 | 2.1 | 1.3
Allergy | 2.2 | 2.3 | 1.0
Insomnia | 1.4 | 2.7 | 0.8
aControlled trials with fluvastatin capsules (20 mg and 40 mg daily and 40 mg twice daily) compared to placebo.
bControlled trials with LESCOL XL 80 mg Tablets as compared to fluvastatin capsules.

In the LESCOL Intervention Prevention Study (LIPS), the effect of LESCOL (fluvastatin capsules) 40 mg, administered twice daily on the risk of recurrent cardiac events was assessed in 1677 patients with coronary heart disease who had undergone a percutaneous coronary intervention. This was a multicenter, randomized, double-blind, placebo-controlled trial, patients were treated with dietary/lifestyle counseling and either fluvastatin capsules 40 mg (n = 844) or placebo (n = 833) given twice daily for a median of 3.9 years [see Clinical Studies (14.3)].Table 2. Adverse Reactions Reported in ≥ 2% in Patients Treated with Fluvastatin Capsules/LESCOL XL and at an Incidence Greater Than Placebo in the LIPS Trial

Table 2. Adverse Reactions Reported in ≥ 2% in Patients Treated with Fluvastatin Capsules/LESCOL XL and at an Incidence Greater Than Placebo in the LIPS Trial
Adverse reaction | Placebo N = 818 (%) | Fluvastatin Capsules 40 mg twice daily N = 822 (%)
Abdominal pain upper | 4.5 | 6.3
Hypertension | 4.2 | 5.8
Fatigue | 3.8 | 4.7
Dyspepsia | 4.0 | 4.5
Edema peripheral | 2.9 | 4.4
Pain in extremity | 2.7 | 4.1
Dizziness | 3.5 | 3.9
Constipation | 2.1 | 3.3
Nasopharyngitis | 2.1 | 2.8
Dyspnea exertional | 2.4 | 2.8
Gastric disorder | 2.1 | 2.7
Nausea | 2.3 | 2.7
Atrial fibrillation | 2.0 | 2.4
Syncope | 2.2 | 2.4
Bronchitis | 2.0 | 2.3
Intermittent claudication | 2.1 | 2.3
Myalgia | 1.6 | 2.2
Arthralgia | 1.8 | 2.1

Elevations in Liver Enzyme Tests

Approximately 1.1% of patients treated with fluvastatin capsules in clinical trials developed dose-related, persistent elevations of serum transaminase levels to more than 3 times the ULN. Fourteen of these patients (0.6%) were discontinued from therapy. In all clinical trials, a total of 33/2969 patients (1.1%) had persistent transaminase elevations with an average fluvastatin exposure of approximately 71.2 weeks; 19 of these patients (0.6%) were discontinued. The majority of patients with these abnormal biochemical findings were asymptomatic.

In a pooled analysis of all placebo-controlled studies in which LESCOL capsules were used, persistent transaminase elevations (> 3 times the ULN on two consecutive weekly measurements) occurred in 0.2%, 1.5%, and 2.7% of patients treated with daily doses of 20, 40, and 80 mg (titrated to 40 mg twice daily) fluvastatin capsules, respectively. Ninety-one percent of the cases of persistent ALT/AST increased abnormalities (20 of 22 patients) occurred within 12 weeks of therapy and in all patients with persistent liver function test abnormalities there was an abnormal liver function test present at baseline or by Week 8.

In the pooled analysis of 24-week controlled trials, persistent transaminase elevation occurred in 1.9%, 1.8%, and 4.9% of patients treated with LESCOL XL 80 mg, fluvastatin capsules 40 mg and fluvastatin capsules 40 mg twice daily, respectively. In 13 of 16 patients treated with LESCOL XL the abnormality occurred within 12 weeks of initiation of treatment with LESCOL XL 80 mg.

6.2 Postmarketing Experience

The following adverse reactions have been identified during postapproval use of fluvastatin. Because these reactions are reported voluntarily from a population of uncertain size, it is not always possible to reliably estimate their frequency or establish a causal relationship to drug exposure.

Musculoskeletal: Muscle cramps, myopathy, rhabdomyolysis, arthralgias, muscle spasms, muscle weakness, myositis. There have been rare reports of IMNM associated with statin use [see Warnings and Precautions (5.2)].

Neurological: Dysfunction of certain cranial nerves (including alteration of taste, impairment of extra-ocular movement, facial paresis), tremor, vertigo, paresthesia, hypoesthesia, dysesthesia, peripheral neuropathy, peripheral nerve palsy. There have been rare postmarketing reports of cognitive impairment (e.g., memory loss, forgetfulness, amnesia, memory impairment, confusion) associated with the use of all statins. The reports are generally nonserious, and reversible upon statin discontinuation, with variable times to symptom onset (1 day to years) and symptom resolution (median of 3 weeks). There have been rare reports of new-onset or exacerbation of myasthenia gravis, including ocular myasthenia, and reports of recurrence when the same or a different statin was administered.

Psychiatric: Anxiety, depression, psychic disturbances

Respiratory: Interstitial lung disease

Hypersensitivity reactions: An apparent hypersensitivity syndrome has been reported rarely which has included one or more of the following features: anaphylaxis, angioedema, lupus erythematosus-like syndrome, polymyalgia rheumatica, vasculitis, purpura, thrombocytopenia, leukopenia, hemolytic anemia, positive ANA, ESR (erythrocyte sedimentation rate) increase, eosinophilia, arthritis, arthralgia, urticaria, asthenia, photosensitivity reaction, fever, chills, flushing, malaise, dyspnea, toxic epidermal necrolysis, erythema multiforme, including Stevens-Johnson syndrome.

Gastrointestinal: Pancreatitis, hepatitis, including chronic active hepatitis, cholestatic jaundice, fatty change in liver, cirrhosis, fulminant hepatic necrosis, hepatoma, anorexia, vomiting, fatal and non-fatal hepatic failure.

Skin: Rash, dermatitis, including bullous dermatitis, eczema, alopecia, pruritus, lichen planus, a variety of skin changes (e.g., nodules, discoloration, dryness of skin/mucous membranes, changes to hair/nails).

Reproductive: Gynecomastia, loss of libido, erectile dysfunction.

Eye: Progression of cataracts (lens opacities), ophthalmoplegia.

Laboratory abnormalities: elevated transaminases, alkaline phosphatase, gamma-glutamyl transpeptidase and bilirubin; thyroid function abnormalities.

7 DRUG INTERACTIONS

7.1 Drug Interactions that Increase the Risk of Myopathy and Rhabdomyolysis with LESCOL XL

Table 3 includes a list of drugs that increase the risk of myopathy and rhabdomyolysis when used concomitantly with fluvastatin and instructions for preventing or managing them [see Warnings and Precautions (5.1), Clinical Pharmacology (12.3)].

Table 3. Drug Interactions That Increase the Risk of Myopathy and Rhabdomyolysis with LESCOL XL

Gemfibrozil
Clinical impact | There is an increased risk of myopathy/rhabdomyolysis when LESCOL XL is administered with gemfibrozil
Intervention | Avoid concomitant use of gemfibrozil with LESCOL XL.
Cyclosporine
Clinical impact | Cyclosporine coadministration increases fluvastatin exposure. The risk of myopathy and rhabdomyolysis may be increased with concomitant use of cyclosporine with LESCOL XL.
Intervention | Avoid concomitant use of cyclosporine with LESCOL XL.
Fluconazole
Clinical impact | Fluconazole coadministration increases fluvastatin exposure. The risk of myopathy and rhabdomyolysis may be increased with concomitant use of fluconazole with LESCOL XL.
Intervention | Avoid concomitant use of fluconazole with LESCOL XL
Niacin
Clinical impact | Risk of myopathy and rhabdomyolysis may be enhanced with concomitant use with lipid-modifying doses (≥ 1 g/day) of niacin with LESCOL XL.
Intervention | Consider if the benefit of using lipid-modifying doses (≥ 1 g/day) of niacin concomitantly with LESCOL XL outweighs the increased risk of myopathy and rhabdomyolysis. If concomitant use is decided, monitor patients for signs and symptoms of myopathy, particularly during initiation of therapy and during upward dose titration.
Fibrates
Clinical impact | Fibrates may cause myopathy when given alone. The risk of myopathy and rhabdomyolysis may be increased with concomitant use of fibrates with LESCOL XL.
Intervention | Consider if the benefit of using fibrates concomitantly with LESCOL XL outweighs the increased risk of myopathy and rhabdomyolysis. If concomitant use is decided, monitor patients for signs and symptoms of myopathy, particularly during initiation of therapy and during upward dose titration.
Colchicine
Clinical impact | Cases of myopathy and rhabdomyolysis have been reported with concomitant use of colchicine with fluvastatin.
Intervention | Consider if the benefit of using colchicine concomitantly with LESCOL XL outweighs the increased risk of myopathy and rhabdomyolysis. If concomitant use is decided, monitor patients for signs and symptoms of myopathy, particularly during initiation of therapy and during upward dose titration.

7.2 LESCOL XL Effects on Other Drugs

Table 4 presents LESCOL XL’s effect on other drugs and instructions for preventing or managing them.

Table 4. LESCOL XL Effects on Other Drugs

Warfarin
Clinical impact | There are postmarketing reports of clinically evident bleeding and/or increased INR in patients taking concomitant statins and warfarin.
Intervention | In patients taking warfarin, obtain an INR before starting LESCOL XL and frequently enough after initiation or discontinuation to ensure that no significant alteration in INR occurs. Once the INR is stable, monitor INR at regularly recommended intervals.
Glyburide
Clinical impact | Concomitant administration of fluvastatin and glyburide increased glyburide exposures [see Clinical Pharmacology (12.3)].
Intervention | Monitor blood glucose levels when LESCOL XL is initiated.
Phenytoin
Clinical impact | Concomitant administration of fluvastatin and phenytoin increased phenytoin exposures [see Clinical Pharmacology (12.3)].
Intervention | Monitor plasma phenytoin levels when LESCOL XL is initiated.

8 USE IN SPECIFIC POPULATIONS

8.1 Pregnancy

Risk Summary

Discontinue LESCOL XL when pregnancy is recognized. Alternatively, consider the ongoing therapeutic needs of the individual patient. LESCOL XL decreases synthesis of cholesterol and possibly other biologically active substances derived from cholesterol; therefore, LESCOL XL may cause fetal harm when administered to pregnant patients based on the mechanism of action [see Clinical Pharmacology (12.1)]. In addition, treatment of hyperlipidemia is not generally necessary during pregnancy. Atherosclerosis is a chronic process and the discontinuation of lipid-lowering drugs during pregnancy should have little impact on the outcome of long-term therapy of primary hyperlipidemia for most patients.

Available data from case series and prospective and retrospective observational cohort studies over decades of use with statins in pregnant women have not identified a drug-associated risk of major congenital malformations. Published data from prospective and retrospective observational cohort studies with LESCOL XL use in pregnant women are insufficient to determine if there is a drug-associated risk of miscarriage (see Data).

In animal reproduction studies, no adverse developmental effects were observed in pregnant rats or rabbits orally administered fluvastatin during the period of organogenesis at doses that resulted in 2 and 5 times, respectively, the human exposure at the maximum recommended human dosage of 40 mg/day, based on body surface area (mg/m^2) (see Data).

The estimated background risk of major birth defects and miscarriage for the indicated population is unknown. In the U.S. general population, the estimated background risk of major birth defects and miscarriage in clinically recognized pregnancies is 2% to 4% and 15% to 20%, respectively.

Data

Human Data

A Medicaid cohort linkage study of 1152 statin-exposed pregnant women compared to 886,996 controls did not find a significant teratogenic effect from maternal use of statins in the first trimester of pregnancy, after adjusting for potential confounders, including maternal age, diabetes mellitus, hypertension, obesity, and alcohol and tobacco use using propensity score-based methods. The relative risk of congenital malformations between the group with statin use and the group with no statin use in the first trimester was 1.07 (95% CI: 0.85 to 1.37) after controlling for confounders, particularly preexisting diabetes mellitus. There were also no statistically significant increases in any of the organ-specific malformations assessed after accounting for confounders. In the majority of pregnancies, statin treatment was initiated prior to pregnancy and was discontinued at some point in the first trimester when pregnancy was identified. Study limitations include reliance on physician coding to define the presence of a malformation, lack of control for certain confounders such as body mass index, use of prescription dispensing as verification for the use of a statin, and lack of information on non-live births.

Animal Data

Fluvastatin sodium given to rats during organogenesis at doses of 12 mg/kg/day and in rabbits at doses of 10 mg/kg/day produced delays in skeletal development. These doses resulted in 2 times (rat at 12 mg/kg) or 5 times (rabbit at 10 mg/kg) the 40 mg human exposure based on mg/m^2 surface area. Malaligned thoracic vertebrae were seen in rats at 36 mg/kg, a dose that produced significant maternal toxicity. A study in which female rats were given fluvastatin during the third trimester at 12 and 24 mg/kg/day resulted in maternal mortality at or near term and postpartum. In addition, fetal and neonatal lethality were apparent. No effects on the dam or fetus occurred at 2 mg/kg/day. A second study at levels of 2, 6, 12 and 24 mg/kg/day confirmed the findings in the first study with neonatal mortality beginning at 6 mg/kg. Rats were given fluvastatin from Gestation Day 15 to Lactation Day 21 at doses of 12 or 24 mg/kg/day with or without the presence of concurrent supplementation with mevalonic acid, a product of HMG-CoA reductase which is essential for cholesterol biosynthesis. The concurrent administration of mevalonic acid completely prevented the maternal and neonatal mortality but did not prevent low body weights in pups at 24 mg/kg on Days 0 and 7 postpartum.

8.2 Lactation

Risk Summary

There is no information about the presence of fluvastatin in human milk, the effects of the drug on the breastfed infant or the effects of the drug on milk production. However, it has been shown that another drug in this class passes into human milk. Studies in rats have shown that fluvastatin and/or its metabolites are present in the milk of lactating rats. When a drug is present in animal milk, it is likely that the drug will be present in human milk (see Data). Statins, including LESCOL XL, decrease cholesterol synthesis and possibly the synthesis of other biologically active substances derived from cholesterol and may cause harm to the breastfed infant.

Because of the potential for serious adverse reactions in a breastfed infant, based on the mechanism of action, advise patients that breastfeeding is not recommended during treatment with LESCOL XL [see Use in Specific Populations (8.1), Clinical Pharmacology (12.1)].

Data

Following a single oral administration of 1 mg/kg of radioactive fluvastatin to lactating rats, the concentration of total radioactivity was determined. Fluvastatin and/or its metabolites were measured in the breast milk at a 2:1 ratio (milk:plasma).

8.4 Pediatric Use

The safety and effectiveness of LESCOL XL as an adjunct to diet to reduce LDL-C have been established in pediatric patients 10 years of age and older with HeFH. Use of LESCOL XL for this indication is based on open-label, uncontrolled clinical trials in 114 pediatric patients 9 years of age and older with HeFH. In these limited uncontrolled studies, there was no significant effect on growth or sexual maturation in the males or females, or on menstrual cycle length in females.

The safety and effectiveness of LESCOL XL have not been established in pediatric patients younger than 10 years of age with HeFH or in pediatric patients with other types of hyperlipidemia (other than HeFH).

8.5 Geriatric Use

Fluvastatin exposures were not significantly different between the nonelderly and elderly populations (age ≥ 65 years) [see Clinical Pharmacology (12.3)].

Advanced age (≥ 65 years) is a risk factor for LESCOL XL-associated myopathy and rhabdomyolysis. Dose selection for an elderly patient should be cautious, recognizing the greater frequency of decreased hepatic, renal, or cardiac function, and of concomitant disease or other drug therapy and the higher risk of myopathy. Monitor geriatric patients receiving LESCOL XL for the increased risk of myopathy [see Warnings and Precautions (5.1)].

8.6 Renal Impairment

Renal impairment is a risk factor for myopathy and rhabdomyolysis. Dose adjustments for mild to moderate renal impairment are not necessary. Fluvastatin has not been studied at doses greater than 40 mg in patients with severe renal impairment; therefore, use LESCOL XL with caution in patients with severe renal impairment. Monitor all patients with renal impairment for development of myopathy [see Warnings and Precautions (5.1), Clinical Pharmacology (12.3)].

8.7 Hepatic Impairment

LESCOL XL is contraindicated in patients with acute liver failure or decompensated cirrhosis [see Contraindications (4), Warnings and Precautions (5.3)].

10 OVERDOSAGE

No specific antidotes for LESCOL XL are known. In the event of an overdose of LESCOL XL, consider contacting the Poison Help line (1-800-222-1222) or a medical toxicologist for additional overdosage management recommendations.

11 DESCRIPTION

Fluvastatin sodium inhibits 3-hydroxy-3-methylglutaryl-coenzyme A (HMG-CoA) reductase.

Fluvastatin sodium is [R*,S*-(E)]-(±)-7-[3-(4-fluorophenyl)-1-(1-methylethyl)-1H-indol-2-yl]-3,5-dihydroxy-6-heptenoic acid, monosodium salt. The empirical formula of fluvastatin sodium is C24H25FNO4•Na, its molecular weight is 433.46 g/mol and its structural formula is:

Fluvastatin sodium is a white to pale yellow, hygroscopic powder soluble in water, ethanol and methanol. LESCOL XL is supplied as extended-release tablets containing 84.24 mg of fluvastatin sodium, equivalent to 80 mg of fluvastatin, for oral use. LESCOL XL tablets contain the following inactive ingredients: hydroxypropyl cellulose, hydroxypropyl methyl cellulose, magnesium stearate, microcrystalline cellulose, polyethylene glycol 8000, potassium bicarbonate, povidone, titanium dioxide, and yellow iron oxide.

12 CLINICAL PHARMACOLOGY

12.1 Mechanism of Action

Fluvastatin is a competitive inhibitor of HMG-CoA reductase, the rate limiting enzyme that converts 3-hydroxy-3-methylglutaryl-coenzyme A (HMG-CoA) to mevalonate, a precursor of cholesterol.

12.2 Pharmacodynamics

Inhibition of HMG-CoA reductase by fluvastatin accelerates the expression of LDL-receptors, followed by the uptake of LDL-C from blood to the liver, leading to a decrease in plasma LDL-C and total cholesterol. Sustained inhibition of cholesterol synthesis in the liver also decreases levels of very-low-density lipoproteins. The maximum LDL-C reduction of LESCOL XL is usually achieved by 4 weeks and is maintained after that.

12.3 Pharmacokinetics

Absorption

Fluvastatin administered as LESCOL XL 80 mg tablets reaches peak concentration in approximately 3 hours under fasting conditions, after a low-fat meal, or 2.5 hours after a low-fat meal. The mean relative bioavailability of the XL tablet is approximately 29% (range, 9% to 66%) compared to that of the fluvastatin immediate-release capsule administered under fasting conditions. Administration of a high-fat meal delayed the absorption (Tmax 6h) and increased the bioavailability of the XL tablet by approximately 50%. However, the maximum concentration of LESCOL XL seen after a high-fat meal is less than the peak concentration following a single dose or twice daily dose of the 40 mg fluvastatin capsule.

Distribution

Fluvastatin is 98% bound to plasma proteins. The mean volume of distribution (VDss) is estimated at 0.35 L/kg. At therapeutic concentrations, the protein binding of fluvastatin is not affected by warfarin, salicylic acid and glyburide.

Elimination

Metabolism

Fluvastatin is metabolized in the liver, primarily via hydroxylation of the indole ring at the 5- and 6-positions. N-dealkylation and beta-oxidation of the side-chain also occurs. The hydroxy metabolites have some pharmacologic activity, but do not circulate in the blood. Fluvastatin has two enantiomers. Both enantiomers of fluvastatin are metabolized in a similar manner.

In vitro data indicate that fluvastatin metabolism involves multiple Cytochrome P450 (CYP) isozymes. CYP2C9 isoenzyme is primarily involved in the metabolism of fluvastatin (approximately 75%), while CYP2C8 and CYP3A4 isoenzymes are involved to a much less extent, i.e., approximately 5% and approximately 20%, respectively.

Excretion

Following oral administration, fluvastatin is primarily (about 90%) excreted in the feces as metabolites, with less than 2% present as unchanged drug. Approximately 5% of a radiolabeled oral dose were recovered in urine. The elimination half-life (t1/2) of fluvastatin is approximately 3 hours.

Specific Populations

Geriatric Patients

Plasma levels of fluvastatin are not significantly different in patients age > 65 years compared to patients age 21 to 49 years.

Gender

In a study evaluating the effect of age and gender on fluvastatin pharmacokinetics, there were no significant differences in fluvastatin exposures between males and females, except between younger females and younger males (both ages 21-49 years), where there was an approximate 30% increase in area under the curve (AUC) in females. Adjusting for body weight decreases the magnitude of the differences seen. For LESCOL XL, the AUC increases 67% and 77% for women compared to men under fasted and high- fat meal fed conditions, respectively.

Pediatric Patients

Pharmacokinetic data in the pediatric population are not available.

Patients with Renal Impairment

In patients with moderate to severe renal impairment (CLCr 10-40 mL/min), AUC and Cmax increased approximately 1.2-fold after administration of a single dose of 40 mg fluvastatin compared to healthy volunteers. In patients with end-stage renal disease on hemodialysis, the AUC increased by approximately 1.5-fold. LESCOL XL was not evaluated in patients with renal impairment [see Use in Specific Populations (8.6)]. However, systemic exposures after administration of LESCOL XL are lower than after the 40 mg immediate release capsule.

Patients with Hepatic Impairment

In patients with hepatic impairment due to liver cirrhosis, fluvastatin AUC and Cmax increased approximately 2.5-fold compared to healthy subjects after administration of a single 40 mg dose [see Use in Specific Populations (8.7)]. The enantiomer ratios of the two isomers of fluvastatin in hepatic impairment patients were comparable to those observed in healthy subjects.

Drug Interaction Studies

Data from drug-drug interactions studies involving coadministration of gemfibrozil, niacin, itraconazole, erythromycin, tolbutamide or clopidogrel indicate that the PK disposition of fluvastatin is not significantly altered when fluvastatin is coadministered with any of these drugs.

The below listed drug interaction information is derived from studies using fluvastatin capsules. Similar studies have not been conducted using the LESCOL XL tablet.

Table 5. Effect of Coadministered Drugs on Fluvastatin Systemic Exposure

Coadministered drug and dosing regimen | Fluvastatin
 | Dose (mg)a | Change in AUCb | Change in Cmaxb
Cyclosporine – stable dose (twice daily)c | 20 mg once daily for 14 weeks | ↑90% | ↑30%
Fluconazole 400 mg once daily; 1,200 mg twice daily 2 to 4c | 40 mg once daily | ↑84% | ↑44%
Cholestyramine 8 g once daily | 20 mg once daily administered 4 hrs after a meal plus cholestyramine | ↓51% | ↓83%
Rifampicin 600 mg once daily for 6 days | 20 mg once daily | ↓53% | ↓42%
Cimetidine 400 mg twice daily for 5 days, once daily on Day 6 | 20 mg once daily | ↑30% | ↑40%
Ranitidine 150 mg twice daily for 5 days, once daily on Day 6 | 20 mg once daily | ↑10% | ↑50%
Omeprazole 40 mg once daily for 6 days | 20 mg once daily | ↑20% | ↑37%
Phenytoin 300 mg once daily | 40 mg twice daily for 5 days | ↑40% | ↑27%
Propranolol 40 mg twice daily for 3.5 days | 40 mg once daily | ↓5% | No change
Digoxin 0.1 to 0.5 mg once daily for 3 weeks | 40 mg once daily | No change | ↑11%
Diclofenac 25 mg once daily | 40 mg once daily for 8 days | ↑50% | ↑80%
Glyburide 5 mg to 20 mg once daily for 22 days | 40 mg twice daily for 14 days | ↑51% | ↑44%
Warfarin 30 mg once daily; Clopidogrel 300 mg loading dose on Day 10, 75 mg once daily on Days 11 to 19 | 40 mg once daily for 8 days; 80 mg XL once daily for 19 days | ↑30%; ↓2% | ↑67%; ↑27%
Abbreviation: AUC, area under the curve.
aSingle dose unless otherwise noted.
bMean ratio (with/without coadministered drug and no change = 1-fold) or % change (with/without coadministered drug and no change = 0%); symbols of ↑ and ↓ indicate the exposure increase and decrease, respectively.
cConsidered clinically significant [see Dosage and Administration (2.4), Drug Interactions (7.1)].

Data from drug-drug interaction studies involving fluvastatin and coadministration of either gemfibrozil, tolbutamide or losartan indicate that the PK disposition of either gemfibrozil, tolbutamide or losartan is not significantly altered when coadministered with fluvastatin.

Table 6. Effect of Fluvastatin Coadministration on Systemic Exposure of Other Drugs
 | Coadministered drug
Fluvastatin dosage regimen | Name and dose (mg)a | Change in AUCb | Change in Cmaxb
40 mg once daily for 5 days | Phenytoin 300 mg once dailyc | ↑20% | ↑5%
40 mg twice daily for 21 days | Glyburide 5 to 20 mg once daily for 22 daysc | ↑70% | ↑50%
40 mg once daily for 8 days | Diclofenac 25 mg once daily | ↑25% | ↑60%
40 mg once daily for 8 days | Warfarin 30 mg once daily | S-warfarin: ↑7%; R-warfarin: no change | S-warfarin: ↑10%; R-warfarin: ↑6%
Abbreviation: AUC, area under the curve.
aSingle dose unless otherwise noted.
bMean ratio (with/without coadministered drug and no change = 1-fold) or % change (with/without coadministered drug and no change = 0%); symbols of ↑ and ↓ indicate the exposure increase and decrease, respectively.
cConsidered clinically significant [see Drug Interactions (7.2)].

13 NONCLINICAL TOXICOLOGY

13.1 Carcinogenesis, Mutagenesis, Impairment of Fertility

In a 2-year carcinogenicity study in rats at doses of 6, 9, and 18 to 24 (escalated after 1 year) mg/kg/day, there was an increased incidence of thyroid follicular cell adenomas and carcinomas in males treated with 18 to 4 mg/kg/day. Additionally, a low incidence of forestomach squamous papillomas and one forestomach carcinoma were observed at the 18 to 24 mg/kg/day dose, likely due to prolonged direct contact exposure rather than a systemic effect. This dose represents a plasma AUC exposure approximately 26 to 35 times the mean human plasma drug concentration after a 40 mg oral dose.

A carcinogenicity study conducted in mice at doses of 0.3, 15 and 30 mg/kg/day revealed a statistically significant increase in forestomach squamous cell papillomas in females at 15 mg/kg/day and in males and females at 30 mg/kg/day. These doses represent plasma AUC exposures approximately 2 and 7 times the mean human plasma drug concentration after a 40 mg oral dose.

No evidence of mutagenicity was observed in vitro, with or without rat-liver metabolic activation, in the following studies: microbial mutagen tests using mutant strains of Salmonella typhimurium or Escherichia coli; malignant transformation assay in BALB/3T3 cells; unscheduled DNA synthesis in rat primary hepatocytes; chromosomal aberrations in V79 Chinese Hamster cells; HGPRT V79 Chinese Hamster cells. In addition, there was no evidence of genotoxicity in vivo in either a rat chromosome aberration study or mouse micronucleus test.

In a fertility study in rats with daily doses up to 6 mg/kg/day for females and 20 mg/kg/day for males, fluvastatin sodium had no adverse effects on the fertility or reproductive performance.

Hamsters treated for 3 months at 20 mg/kg/day (approximately three times the 40 mg human daily dose based on body surface area, mg/m^2) showed small seminal vesicles and testes, along with tubular degeneration and aspermatogenesis in the testes and vesiculitis in the seminal vesicles. Rats treated for 2 years at 18 mg/kg/day (approximately four times human exposure based on body surface area) exhibited vesiculitis in the seminal vesicles and edema in the testes.

14 CLINICAL STUDIES

Secondary Prevention of Cardiovascular Disease

In the LESCOL Intervention Prevention Study (LIPS), the effect of fluvastatin capsules 40 mg administered twice daily on the risk of recurrent cardiac events (time to first occurrence of cardiac death, nonfatal myocardial infarction, or revascularization) was assessed in 1677 adult patients with CHD who had undergone a percutaneous coronary intervention (PCI) procedure (mean time from PCI to randomization = 3 days). In this multicenter, randomized, double-blind, placebo-controlled trial, patients were treated with dietary/lifestyle counseling and either fluvastatin 40 mg (n = 844) or placebo (n = 833) given twice daily for a median of 3.9 years. The study population was 84% male, 98% White, with 37% > 65 years of age. Mean baseline lipid concentrations were: total cholesterol 201 mg/dL, LDL-C 132 mg/dL, triglycerides 70 mg/dL, and HDL-C 39 mg/dL.

Fluvastatin capsules significantly reduced the risk of recurrent cardiac events (Figure 1) by 22% (p = 0.013, 181 patients in the fluvastatin capsules group versus 222 patients in the placebo group). Revascularization procedures comprised the majority of the initial recurrent cardiac events (143 revascularization procedures in the fluvastatin capsules group and 171 in the placebo group). Consistent trends in risk reduction were observed in patients > 65 years of age.

Figure 1. Primary Endpoint – Recurrent Cardiac Events (Cardiac Death, Nonfatal MI or Revascularization Procedure) (ITT Population)

Outcome data for the LESCOL Intervention Prevention Study are shown in Figure 2. After exclusion of revascularization procedures (CABG and repeat PCI) occurring within the first 6 months of the initial procedure involving the originally instrumental site, treatment with fluvastatin capsules was associated with a 32% (p = 0.002) reduction in risk of late revascularization procedures (CABG or PCI occurring at the original site > 6 months after the initial procedure, or at another site).

Figure 2. LESCOL Intervention Prevention Study–- Primary and Secondary Endpoints

In the Lipoprotein and Coronary Atherosclerosis Study (LCAS), the effect of fluvastatin capsule therapy on coronary atherosclerosis was assessed by quantitative coronary angiography (QCA) in patients with CAD and mild to moderate hypercholesterolemia (baseline LDL-C range 115 to 190 mg/dL). In this randomized double-blind, placebo-controlled trial, 429 patients were treated with conventional measures (Step 1, AHA Diet) and either fluvastatin 40 mg/day or placebo. In order to provide treatment to patients receiving placebo with LDL-C levels ≥160 mg/dL at baseline, adjunctive therapy with cholestyramine was added after Week 12 to all patients in the study with baseline LDL-C values of ≥ 160 mg/dL, which were present in 25% of the study population. Quantitative coronary angiograms were evaluated at baseline and 2.5 years in 340 (79%) angiographic evaluable patients.

Compared to placebo, fluvastatin capsules significantly slowed the progression of coronary atherosclerosis as measured by within-patient per-lesion change in minimum lumen diameter (MLD), the primary endpoint (Figure 3 below), percent diameter stenosis (Figure 4), and the formation of new lesions (13% of all fluvastatin patients versus 22% of all placebo patients). A significant difference in favor of fluvastatin capsules was found between all fluvastatin and all placebo patients in the distribution among the three categories of definite progression, definite regression, and mixed or no change. Beneficial angiographic results (change in MLD) were independent of patients’ gender and consistent across a range of baseline LDL-C levels.

Figure 3. Change in Minimum Lumen Diameter (mm)

Figure 4. Change in % Diameter Stenosis

Primary Hyperlipidemia in Adults

LESCOL XL has been studied in five controlled trials of adult patients with primary hyperlipidemia and mixed dyslipidemia. LESCOL XL was administered to over 900 patients in trials from 4 to 26 weeks in duration. In the three largest of these trials, LESCOL XL given as a single daily dose of 80 mg significantly reduced Total-C, LDL-C, TG, and Apo B (Table 5).

In patients with primary mixed dyslipidemia as defined by baseline plasma TG levels ≥ 200 mg/dL and < 400 mg/dL, treatment with LESCOL XL produced significant decreases in Total-C, LDL-C, TG, and Apo B (see Table 7).

Table 7. Median Percent Change in Lipid Levels in Adult Patients with Primary Hyperlipidemia and Mixed Dyslipidemia From Baseline to Week 24 Endpoint All Active Controlled Trials (LESCOL XL)

 | Total Chol |  | TG |  | LDL |  | Apo B |  | HDL
Dose | N | %∆ | N | %∆ | N | %∆ | N | %∆ | N | %∆
All Patients
LESCOL XL 80 mga | 750 | -25 | 750 | -19 | 748 | -35 | 745 | -27 | 750 | +7
Baseline TG ≥ 200 mg/dL
LESCOL XL 80 mga | 239 | -25 | 239 | -25 | 237 | -33 | 235 | -27 | 239 | +11
aData for LESCOL XL 80 mg tablet from three 24- week controlled trials.

HeFH in Pediatric Patients Aged 10 Years and Older

Fluvastatin capsules were studied in two open-label, uncontrolled, dose-titration trials. The first trial enrolled 29 pre-pubertal males, 9 to12 years of age, who had an LDL-C level > 90th percentile for age and one parent with primary hypercholesterolemia and either a family history of premature ischemic heart disease or tendon xanthomas. The mean baseline LDL-C was 226 mg/dL (range, 137 to 354 mg/dL). All patients were started on fluvastatin capsules 20 mg daily with dose adjustments every 6 weeks to 40 mg daily then 80 mg daily (40 mg twice daily) to achieve an LDL-C goal between 97 to 124 mg/dL. Endpoint analyses were performed at Year 2. Fluvastatin decreased plasma levels of Total-C and LDL-C by 21% and 27%, respectively. The mean achieved LDL-C was 161 mg/dL (range, 74 to 336 mg/dL).

The second trial enrolled 85 male and female patients, 10 to 16 years of age, who had an LDL-C > 190 mg/dL or LDL-C > 160 mg/dL and one or more risk factors for coronary heart disease, or LDL-C > 160 mg/dL and a proven LDL-receptor defect. The mean baseline LDL-C was 225 mg/dL (range, 148 to 343 mg/dL). All patients were started on fluvastatin capsules 20 mg daily with dose adjustments every 6 weeks to 40 mg daily then 80 mg daily (LESCOL XL tablet) to achieve an LDL-C goal of < 130 mg/dL. Endpoint analyses were performed at Week 114. Fluvastatin decreased plasma levels of Total-C and LDL-C by 22% and 28%, respectively. The mean achieved LDL-C was 159 mg/dL (range, 90 to 295 mg/dL).

The majority of patients in both trials (83% in the first trial and 89% in the second trial) were titrated to the maximum daily dose of 80 mg.

16 HOW SUPPLIED/STORAGE AND HANDLING

How Supplied

LESCOL XL extended-release tablets supplied as:

Strength | How supplied | NDC | Tablet description
80 mg of fluvastatin | bottles of 30 | 66758-211-31 | Yellow, round, slightly biconvex film-coated tablet with beveled edges debossed with “LESCOL XL” on one side and “80” on the other

Store and Dispense

Store at 20ºC to 25ºC (68ºF to 77ºF); excursions permitted between 15ºC to 30ºC (59ºF to 86ºF) [see USP Controlled Room Temperature]. Dispense in a tight container. Protect from light.

17 PATIENT COUNSELING INFORMATION

Advise the patient to read the FDA-approved patient labeling (Patient Information).

Myopathy and Rhabdomyolysis

Advise patients that LESCOL XL may cause myopathy and rhabdomyolysis. Instruct patients to promptly report any unexplained muscle pain, tenderness, or weakness particularly if accompanied by malaise or fever [see Warnings and Precautions (5.1), Drug Interactions (7.1)].

Hepatic Dysfunction

Inform patients that LESCOL XL may cause liver enzyme elevations and possibly liver failure. Advise patients to promptly report fatigue, anorexia, right upper abdominal discomfort, dark urine, or jaundice [see Warnings and Precautions (5.3)].

Increases in HbA1c and Fasting Serum Glucose Levels

Inform patients that increases in HbA1c and fasting serum glucose levels may occur with LESCOL XL. Encourage patients to optimize lifestyle measures, including regular exercise, maintaining a healthy body weight, and making healthy food choices [see Warnings and Precautions (5.4)].

Pregnancy

Advise pregnant patients and patients who can become pregnant of the potential risk to a fetus. Advise patients to inform their healthcare provider of a known or suspected pregnancy to discuss if LESCOL XL should be discontinued [see Use in Specific Populations (8.1)].

Lactation

Advise patients that breastfeeding is not recommended during treatment with LESCOL XL [see Use in Specific Populations (8.2)].

Manufactured by

Pfizer Ireland Pharmaceuticals

Newbridge, Ireland for

Sandoz Inc., Princeton, NJ 08540

PATIENT INFORMATION

LESCOL® XL(lĕs-cŏl)

(fluvastatin)

extended-release tablets, for oral use

You must read and follow all instructions before using LESCOL XL.

Read this Patient Information before you start taking LESCOL XL and each time you get a refill. There may be new information. This information does not take the place of talking with your healthcare provider about your medical condition or your treatment. If you have any questions about LESCOL XL, ask your doctor or pharmacist.

What is LESCOL XL?

LESCOL XL is a prescription medicine “that contains the cholesterol lowering medicine, fluvastatin.”

LESCOL XL is used in adults with heart disease (coronary artery disease) to:

- lower the need for heart and blood vessel procedures to improve flow to the heart, called coronary revascularization.
- slow the buildup of too much cholesterol in the arteries of the heart.

LESCOL XL is used along with diet to lower the level of:

- low-density lipoprotein cholesterol (LDL-C) or “bad” cholesterol in adults with hyperlipidemia (high levels of fat in the blood)
- LDL-C in adults and children 10 years of age and older with heterozygous familial hypercholesterolemia (HeFH), an inherited condition that causes high levels of LDL, who require 80 mg of fluvastatin daily.

The safety and effectiveness of LESCOL XL has not been established in children younger than 10 years of age with heterozygous familial hypercholesterolemia (HeFH) or in children with other types of hyperlipidemia (high levels in fat in the blood) other than HeFH.

Do not take LESCOL XL if you:

- have liver problems (acute liver failure or decompensated cirrhosis)
- are allergic to fluvastatin or any of the ingredients in LESCOL XL. See the end of this Patient Information leaflet for a complete list of ingredients in LESCOL XL.

Before you take LESCOL XL, tell your healthcare provider about all of your medical conditions, including if you:

- have muscle aches or weakness
- drink more than 2 glasses of alcohol daily
- have diabetes
- have a thyroid problem
- have kidney problems
- are pregnant or plan to become pregnant. If you become pregnant while taking LESCOL XL, stop taking LESCOL XL and call your healthcare provider.
- are breastfeeding or plan to breastfeed. It is not known if LESCOL XL passes into your breast milk. Talk to your healthcare provider about the best way to feed your baby if you take LESCOL XL. You should not breastfeed while taking LESCOL XL

Tell your healthcare provider about all the medicines you take, including prescription and over-the-counter medicines, vitamins, and herbal supplements. Talk to your healthcare provider before you start taking any new medicines. Tell your healthcare provider who prescribes LESCOL XL if another healthcare provider increases the dose of another medicine you are taking.

LESCOL XL may affect the way other medicines work, and other medicines may affect how LESCOL XL works. Especially tell your healthcare provider if you take:

- warfarin (a medicine used to reduce blood clotting)
- glyburide (a medicine used to treat diabetes)
- phenytoin (a medicine used to treat epilepsy)

Taking LESCOL XL with certain medicines can also increase the risk of muscle problems. Especially tell your healthcare provider if you take:

- gemfibrozil (a medicine used to lower triglycerides)
- cyclosporine (a medicine used to suppress the immune system)
- fluconazole (a medicine used to treat fungal infections)
- fibrates or niacin
- colchicine

Ask your healthcare provider or pharmacist for a list of medicines if you are not sure. Know the medicines you take. Keep a list of them to show your healthcare provider and pharmacist when you get a new medicine.

How should I take LESCOL XL?

- Take LESCOL XL exactly as your healthcare provides tells you to take it.
- Do not change your dose or stop taking LESCOL XL without talking to your healthcare provider.
- Take LESCOL XL tablets 1 time each day, at any time of the day. LESCOL XL can be taken with or without food.
- LESCOL XL tablets must be swallowed whole with a liquid. Do not break, crush or chew LESCOL XL tablets. Tell your healthcare provider if you cannot swallow tablets whole. You may need fluvastatin capsules or a different medicine instead of LESCOL XL tablets.
- While taking LESCOL XL, continue to follow your cholesterol-lowing diet and exercise as your healthcare provider told you to.
- In case of overdose, get medical help or contact a Poison Center expert right away at 1-800-222-1222. Advice is also available online at poisonhelp.org.

What are the possible side effects of LESCOL XL?

LESCOL XL may cause serious side effects, including:

- Muscle pain, tenderness, and weakness (myopathy). Muscle problems, including muscle breakdown, can be serious in some people and rarely cause kidney damage that can lead to death.

Tell your healthcare provider right away if you have:

- unexplained muscle pain, tenderness, or weakness, especially if you have a fever or feel more tired than usual, while you take LESCOL XL.
- muscle problems that do not go away even after your healthcare provider has advised you to stop taking LESCOL XL. Your healthcare provider may do further tests to diagnose the cause of your muscle problems. Your chances of getting muscle problems are higher if you:
- are taking certain other medicines while you take LESCOL XL
- are 65 years of age or older
- have thyroid problems (hypothyroidism) that are not controlled
- have kidney problems
- Liver problems. Your healthcare provider should do blood tests to check your liver before you start taking LESCOL XL, and if you have symptoms of liver problems while you take LESCOL XL. Call your healthcare provider right away if you have the following symptoms of liver problems:
- feel tired or weak
- loss of appetite
- right sided upper belly pain
- dark amber colored urine
- yellowing of your skin or the whites of your eye
- Increase in blood sugar (glucose) levels. LESCOL XL may cause an increase in your blood sugar levels.

The most common side effects of LESCOL XL include:

- flu-like symptoms
- sinus infection
- upset stomach and stomach pain
- urinary tract infections
- bronchitis
- nausea

These side effects are usually mild and may go away. The following additional side effects have been reported with LESCOL XL:

- memory loss and confusion

Talk to your healthcare provider or pharmacist if you have side effects that bother you or does not go away.

These are not all the possible side effects of LESCOL XL. Call your healthcare provider for medical advice about side effects. You may report side effects to the FDA at 1-800-FDA-1088.

How should I store LESCOL XL?

- Store LESCOL XL at room temperature 68°F to 77°F (20°C to 25°C). Protect from light.
- Keep LESCOL XL out of the reach of children. Be sure that if you throw medicines away, it is out of the reach of children.

General information about safe and effective use of LESCOL XL.

Medicines are sometimes prescribed for purposes other than those listed in a Patient Information Leaflet. Do not use LESCOL XL for a condition for which it was not prescribed. Do not give LESCOL XL to other people, even if they have the same medical condition you have; it may harm them.

You can ask your pharmacist or healthcare provider for information about LESCOL XL that is written for health professionals.

What are the ingredients in LESCOL XL?

Active Ingredient: fluvastatin

Inactive Ingredients: hydroxypropyl cellulose, hydroxypropyl methyl cellulose, magnesium stearate, microcrystalline cellulose, polyethylene glycol 8000, potassium bicarbonate, povidone, titanium dioxide, and yellow iron oxide.

For more information go to www.sandoz.com or call 1-800-525-8747.

Manufactured by

Pfizer Ireland Pharmaceuticals

Newbridge, Ireland for

Sandoz Inc., Princeton, NJ 08540

This Patient Information has been approved by the U.S. Food and Drug Administration. Revised: 12/2023

PRINCIPAL DISPLAY PANEL

NOVARTIS

NDC 66758-211-31

Lescol® XL
(fluvastatin sodium)

Extended-Release Tablets

equivalent to
80 mg per tablet
fluvastatin

30 tablets

Rx only